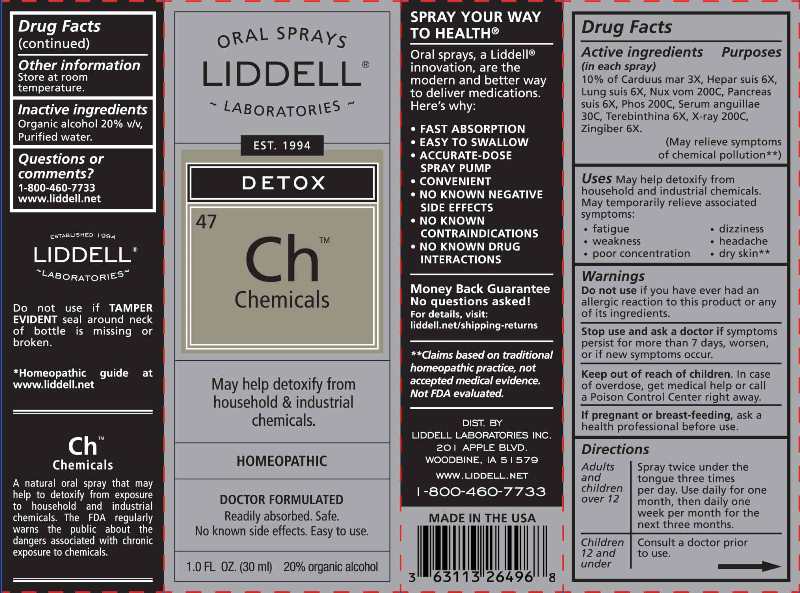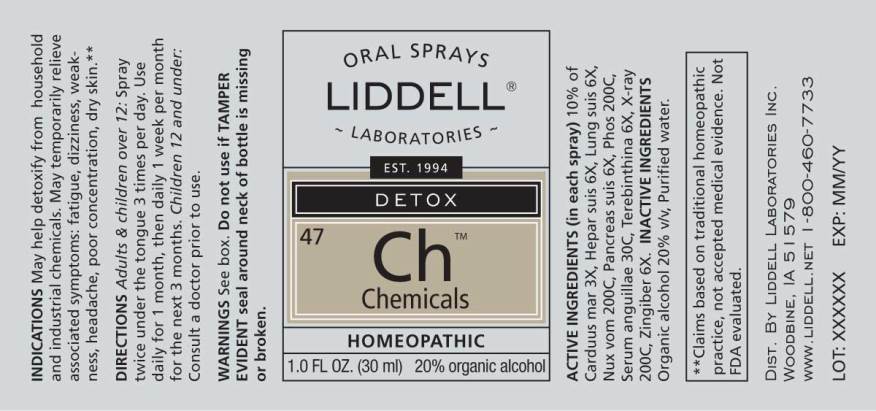 DRUG LABEL: Chemicals
NDC: 50845-0250 | Form: SPRAY
Manufacturer: Liddell Laboratories, Inc.
Category: homeopathic | Type: HUMAN OTC DRUG LABEL
Date: 20230622

ACTIVE INGREDIENTS: SILYBUM MARIANUM SEED 3 [hp_X]/1 mL; PORK LIVER 6 [hp_X]/1 mL; SUS SCROFA LUNG 6 [hp_X]/1 mL; STRYCHNOS NUX-VOMICA SEED 200 [hp_C]/1 mL; SUS SCROFA PANCREAS 6 [hp_X]/1 mL; PHOSPHORUS 200 [hp_C]/1 mL; ANGUILLA ROSTRATA BLOOD SERUM 30 [hp_C]/1 mL; TURPENTINE OIL 6 [hp_X]/1 mL; ALCOHOL, X-RAY EXPOSED (1000 RAD) 200 [hp_C]/1 mL; GINGER 6 [hp_X]/1 mL
INACTIVE INGREDIENTS: WATER; ALCOHOL

Drug Facts:

ACTIVE INGREDIENTS:

(in each spray) 10% of Carduus Marianus 3X, Hepar Suis 6X, Lung Suis 6X, Nux Vomica 200C, Pancreas Suis 6X, Phosphorus 200C, Serum Anguillae 30C, Terebinthina 6X, X-Ray 200C, Zingiber Officinale 6X.

USES:

May help detoxify from household and industrial chemicals. May temporarily relieve associated symptoms:

• fatigue

• dizziness

• weakness

• headache

• poor concentration

• dry skin**

**Claims based on traditional homeopathic practice, not accepted medical evidence. Not FDA evaluated.

WARNINGS:

Do not use if you have ever had an allergic reaction to this product or any of its ingredients.

Stop use and ask a doctor if symptoms persist for more than 7 days, worsen or if new symptoms occur.

Keep out of reach of children. In case of overdose, get medical help or call a Poison Control Center right away.

If pregnant or breast feeding, ask a health professional before use.

Store at room temperature.

Do not use if TAMPER EVIDENT seal around neck of bottle is missing or broken.

Keep out of reach of children. In case of overdose, get medical help or call a Poison Control Center right away.

DIRECTIONS:

Adults and Children over 12:

Spray twice under the tongue three times per day. Use daily for one month, then daily one week per month for the next three months.

Children 12 and under

Consult a doctor prior to use.

USES:

May help detoxify from household and industrial chemicals. May temporarily relieve associated symptoms:

• fatigue

• dizziness

• weakness

• headache

• poor concentration

• dry skin**

**Claims based on traditional homeopathic practice, not accepted medical evidence. Not FDA evaluated.

INACTIVE INGREDIENTS:

Organic alcohol 20% v/v, Purified water.

QUESTIONS:

DIST BY

LIDDELL LABORATORIES INC.

201 APPLE BLVD.

WOODBINE, IA 51579

www.LIDDELL.NET

1-800-460-7733

PACKAGE DISPLAY LABEL:

ORAL SPRAYS
LIDDELL
LABORATORIES

EST. 1994

DETOX

^47 Ch
Chemicals

May help detoxify from household &
industrial chemicals.

HOMEOPATHIC
DOCTOR FORMULATED

Readily absorbed. Safe.
No known side effects. Easy to use.

1.0 FL OZ (30 ml)